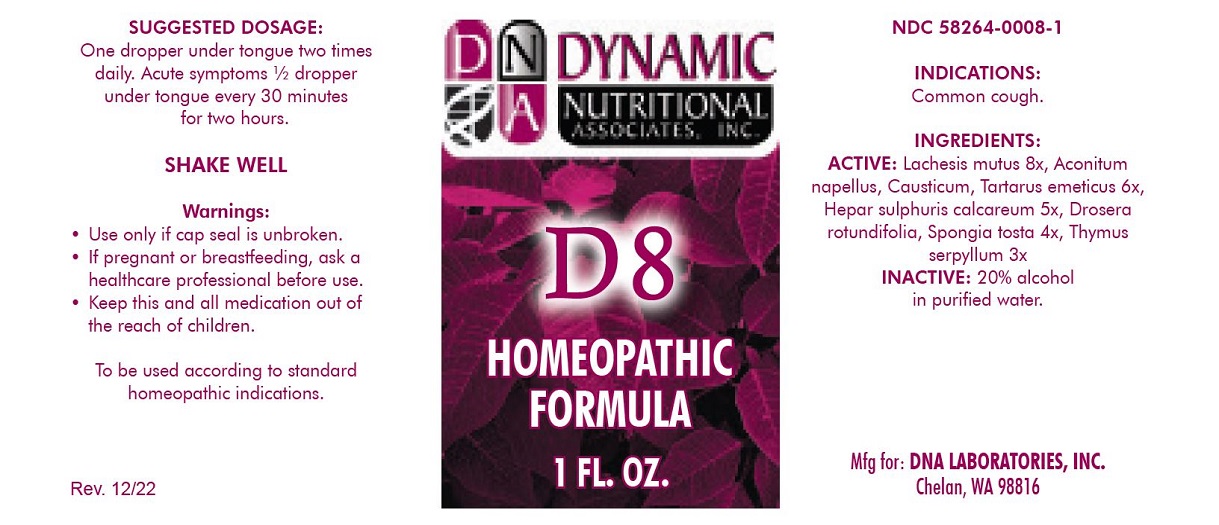 DRUG LABEL: D-8
NDC: 58264-0008 | Form: SOLUTION
Manufacturer: DNA Labs, Inc.
Category: homeopathic | Type: HUMAN OTC DRUG LABEL
Date: 20250113

ACTIVE INGREDIENTS: SPONGIA OFFICINALIS SKELETON, ROASTED 4 [hp_X]/1 mL; CAUSTICUM 6 [hp_X]/1 mL; LACHESIS MUTA VENOM 8 [hp_X]/1 mL; CALCIUM SULFIDE 5 [hp_X]/1 mL; THYMUS SERPYLLUM 3 [hp_X]/1 mL; ANTIMONY POTASSIUM TARTRATE 6 [hp_X]/1 mL; ACONITUM NAPELLUS 6 [hp_X]/1 mL; DROSERA ROTUNDIFOLIA 4 [hp_X]/1 mL
INACTIVE INGREDIENTS: ALCOHOL; WATER

D-8

NDC 58264-0008-1

INDICATIONS

PURPOSE

Common cough.

INGREDIENTS

ACTIVE

Spongia tosta 4x, Causticum 6x, Lachesis mutus 8x, Hepar sulphuris calcareum 5x, Thymus serpyllum 3x, Tartarus emeticus 6x, Aconitum napellus 6x, Drosera rotundifolia 4x

INACTIVE

20% alcohol in purified water.

SUGGESTED DOSAGE

One dropper under tongue two times daily. Acute symptoms ½ dropper under tongue every 30 minutes for two hours.

STORAGE AND HANDLING

SHAKE WELL

Warnings

- Use only if cap seal is unbroken.

PREGNANCY OR BREAST FEEDING

- If pregnant or breastfeeding, ask a healthcare professional before use.

KEEP OUT OF REACH OF CHILDREN

- Keep this and all medication out of the reach of children.

To be used according to standard homeopathic indications.

PRINCIPAL DISPLAY PANEL - 1 FL. OZ. Bottle Label

DYNAMIC
NUTRITIONAL
ASSOCIATES, INC.

D 8

HOMEOPATHIC
STRESS FORMULA

1 FL. OZ.